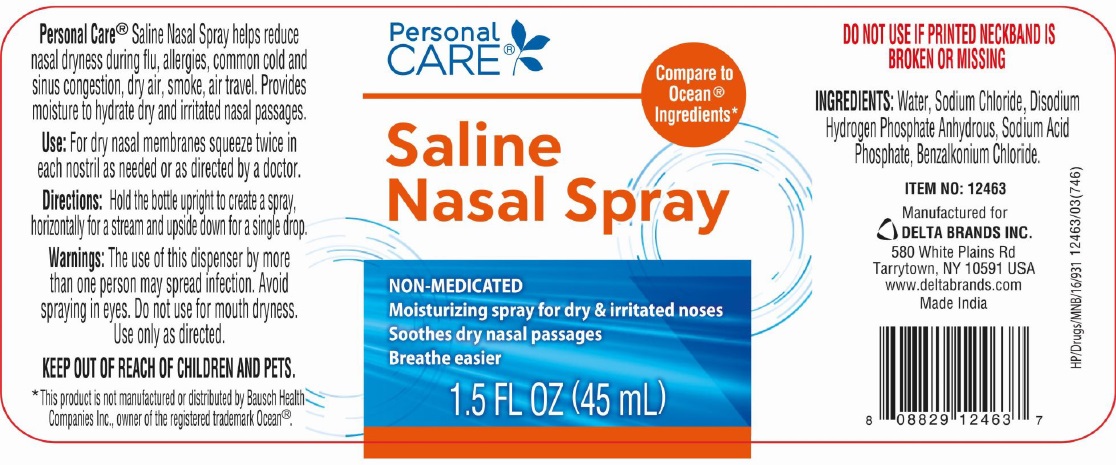 DRUG LABEL: Saline 1.5 FL OZ
NDC: 73492-251 | Form: SPRAY
Manufacturer: ALAINA HEALTHCARE PRIVATE LIMITED
Category: otc | Type: HUMAN OTC DRUG LABEL
Date: 20250519

ACTIVE INGREDIENTS: SODIUM CHLORIDE 65 g/1 mL
INACTIVE INGREDIENTS: WATER; SODIUM PHOSPHATE, DIBASIC, ANHYDROUS; SODIUM PHOSPHATE, MONOBASIC, ANHYDROUS; BENZALKONIUM CHLORIDE

Saline Nasal Spray 1.5 FL OZ (45 mL)
NON-MEDICATED
Moisturizing spray for dry & irritated noses
Soothes dry nasal passages
Breathe easier

Personal Care®Saline Nasal Spray helps reduce nasal dryness during flu, allergies, common cold and sinus congestion, dry air, smoke, air travel. Provides moisture to hydrate dry and irritated nasal passages.

Use

For dry nasal membranes squeeze twice in each nostril as needed or as directed by a doctor.

Directions

Hold the bottle upright to create a spray, Horizontally for a stream and upside down for a single drop.

Warnings

The use of this dispenser by more than one person may spread infection. Avoid spraying in eyes. Do not use for mouth dryness. Use only as directed.

KEEP OUT OF REACH OF CHILDREN AND PETS

INGREDIENTS

Water, Sodium Chloride, Disodium Hydrogen Phosphate Anhydrous, Sodium Acid Phosphate, Benzalkonium Chloride.

PRINCIPAL DISPLAY PANEL

Saline Nasal Spray 1.5 FL OZ (45mL) - NDC 73492-251-45 - Bottle Label